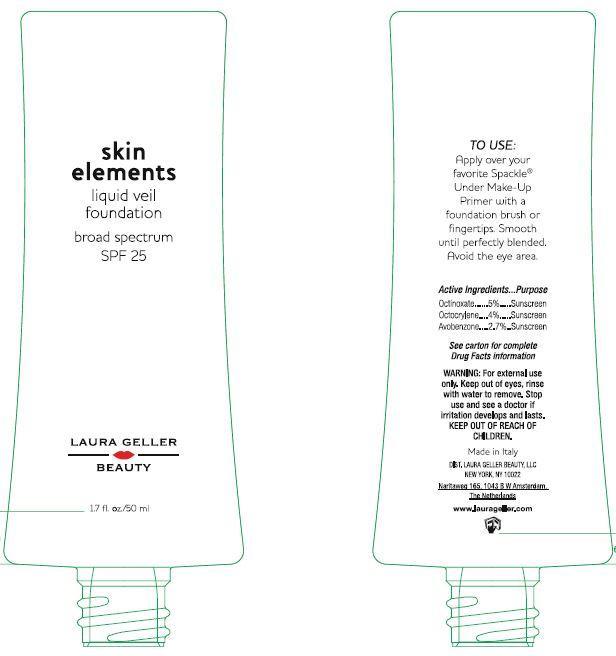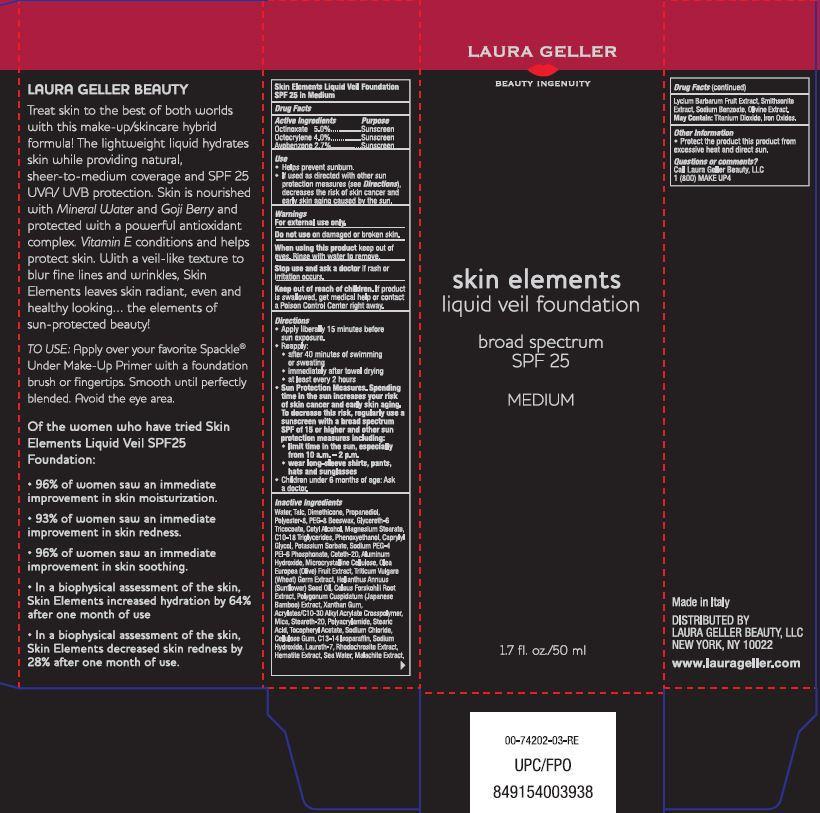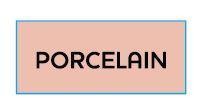 DRUG LABEL: skin elements liquid veil foundation broad spectrum SPF 25
NDC: 51389-253 | Form: CREAM
Manufacturer: Laura Geller Beauty, LLC
Category: otc | Type: HUMAN OTC DRUG LABEL
Date: 20191226

ACTIVE INGREDIENTS: OCTINOXATE 50 mg/1 mL; OCTOCRYLENE 40 mg/1 mL; AVOBENZONE 27 mg/1 mL
INACTIVE INGREDIENTS: WATER; TALC; DIMETHICONE; PROPANEDIOL; POLYETHYLENE GLYCOL 400; YELLOW WAX; GLYCERETH-6; CETYL ALCOHOL; MAGNESIUM STEARATE; C10-18 TRIGLYCERIDES; PHENOXYETHANOL; CAPRYLYL GLYCOL; POTASSIUM SORBATE; CETETH-20; ALUMINUM HYDROXIDE; CELLULOSE, MICROCRYSTALLINE; BLACK OLIVE; WHEAT GERM; SUNFLOWER OIL; PLECTRANTHUS BARBATUS ROOT; POLYGONUM CUSPIDATUM LEAF; XANTHAN GUM; MICA; STEARETH-20; STEARIC ACID; .ALPHA.-TOCOPHEROL ACETATE; SODIUM CHLORIDE; CARBOXYMETHYLCELLULOSE SODIUM; C13-14 ISOPARAFFIN; SODIUM HYDROXIDE; LAURETH-7; LYCIUM BARBARUM FRUIT; SODIUM BENZOATE; TITANIUM DIOXIDE; FERRIC OXIDE RED

skin elements liquid veil foundation broad spectrum SPF 25 GOLDEN MEDIUM

Active Ingredients

Octinoxate 5.0%
Octocrylene 4.0%
Avobenzone 2.7%

Purpose

Sunscreen

Use

- Helps prevent sunburn.
- If used as directed with other sun protection measures (see Directions), decreases the risk of skin cancer and early skin aging caused by the sun.

Warnings

For external use only.

Do not use

on damaged or broken skin.

When using this product

keep out of eyes. Rinse with water to remove.

Stop use and ask a doctor

if rash or irritation occurs

Keep out of reach of children.

If product is swallowed, get medical help or contact a Poison Control Center right away.

Directions

- Apply liberally 15 minutes before sun exposure.
- Reapply:
  - after 40 minutes of swimming or sweating
  - immediately after towel drying
  - at least every 2 hours
- Sun Protection Measures. Spending time in the sun increases your risk of skin cancer and early skin aging. To decrease this risk, regularly use a sunscreen with a broad spectrum SPF of 15 or higher and other sun protection measures including:
  - limit time in the sun, especially from 10 a.m. – 2 p.m.
  - wear long-sleeve shirts, pants, hats and sunglasses
- Children under 6 months of age: Ask a doctor.

Inactive Ingredients

Water, Talc, Dimethicone, Propanediol, Polyester-8, PEG-8 Beeswax, Glycereth-6 Tricocoate, Cetyl Alcohol, Magnesium Stearate, C10-18 Triglycerides, Phenoxyethanol, Caprylyl Glycol, Potassium Sorbate, Sodium PEG-4 PEI-6 Phosphonate, Ceteth-20, Aluminum Hydroxide, Microcrystalline Cellulose, Olea Europea (Olive) Fruit Extract, Triticum Culgare (Wheat) Germ Extract, Helianthus Annuus (Sunflower) Seed Oil, Coleus Forskohilii Root Extract, Polygonum Cuspidatum (Japanese Bamboo) Extract, Xanthan Gum, Acrylates/C10-30 Alkyl Acrylate Crosspolymer, Mica, Steareth-20, Polyacrylamide, Stearic Acid, Tocopheryl Acetate, Sodium Chloride, Cellulose Gum, C13-13 Isoparaffin, Sodium Hydroxide, Laureth-7, Rhodochrosite Extract, Hematite Extract, Sea Water, Malachite Extract, Lycium Barbarum Fruit Extract, Smithsonite Extract, Sodium Benzoate, Olivine Extract. May Contain: Titanium Dioxide, Iron Oxides.

Other Information

- Protect the product this product from excessive heat and direct sun.

Questions or comments?

Call Laura Geller Beauty, LLC
1 (800) MAKE UP4

Carton Package Label

LAURA GELLER
BEAUTY INGENUITY

skin elements
liquid veil foundation

broad spectrum
SPF 25

GOLDEN MEDIUM

1.7 fl. oz./50 ml

Treat skin to the best of both worlds with this make-up/skincare hybrid formula! The lightweight liquid hydrates kin while providing natural, sheer-to-medium coverage and SPF 25 UVA/UVB protection. Skin is nourished with Mineral Water and Goji Berry and protected with a powerful antioxidant complex. Vitamin E conditions and helps protect skin. with a veil-like texture to blur fine lines and wrinkles, Skin Elements leaves skin radiant, even and healthy looking... the elements of sun-protected beauty!

TO USE: Apply over your favorite Spackle®
Under Make-Up Primer with a foundation brush or fingertips. Smooth until perfectly blended. Avoid the eye area.

Of the women who have tried Skin Elements Liquid Veil SPF25 Foundation:

- 96% of women saw an immediate improvement in skin moisturization.
- 93% of women saw an immediate improvement in skin redness.
- 96% of women saw an immediate improve in skin soothing.
- In a biophysical assessment of the skin, Skin Elements increased hydration by 64% after one month of use
- In a biophysical assessment of the skin, Skin Elements decreased skin redness by 28% after one month of use.

Made in Italy

DISTRIBUTED BY
LAURA GELLER BEAUTY, LLC
NEW YORK, NY 10022

www.laurageller.com

00-74202-04-RE

UPC/FPO

849154003945

Bottle Label

See carton for complete
Drug Facts information

Naritaweg 165, 1043 B W Amsterdam

The Netherlands